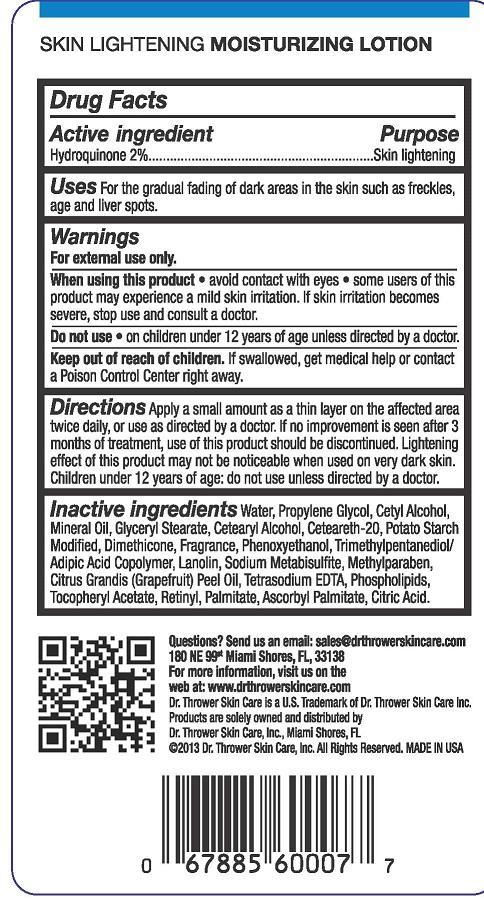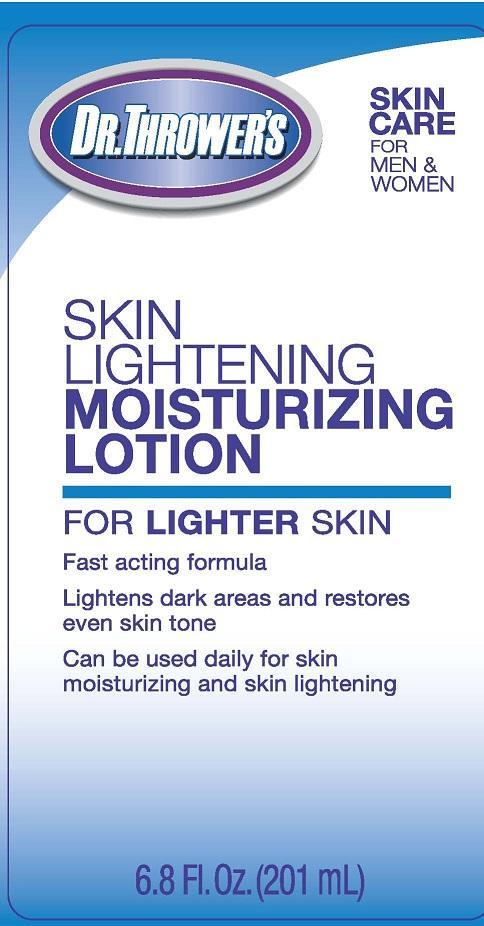 DRUG LABEL: DR. THROWERS SKIN LIGHTENING MOISTURIZING
NDC: 69299-302 | Form: LOTION
Manufacturer: DR. THROWER'S SKINCARE, INC.
Category: otc | Type: HUMAN OTC DRUG LABEL
Date: 20150522

ACTIVE INGREDIENTS: HYDROQUINONE 2 g/100 mL
INACTIVE INGREDIENTS: WATER; PROPYLENE GLYCOL; CETYL ALCOHOL; MINERAL OIL; GLYCERYL MONOSTEARATE; CETOSTEARYL ALCOHOL; CETEARETH-22; STARCH, POTATO; DIMETHICONE; PHENOXYETHANOL; TRIMETHYLPENTANEDIOL/ADIPIC ACID/GLYCERIN CROSSPOLYMER (25000 MPA.S); LANOLIN; SODIUM METABISULFITE; METHYLPARABEN; GRAPEFRUIT PEEL; EDETATE SODIUM TETRAHYDRATE; EGG PHOSPHOLIPIDS; .ALPHA.-TOCOPHEROL ACETATE; VITAMIN A PALMITATE; ASCORBYL PALMITATE; ANHYDROUS CITRIC ACID

ACTIVE INGREDIENT

HYDROQUINONE 2%

PURPOSE

SKIN LIGHTENING

USES:

FOR THE GRADUAL FADING OF DARK AREAS IN THE SKIN SUCH AS FRECKLES, AGE AND LIVER SPOTS.

WARNINGS

FOR EXTERNAL USE ONLY.

WHEN USING THIS PRODUCT

- AVOID CONTACT WITH EYES.
- SOME USERS OF THIS PRODUCT MAY EXPERIENCE SKIN IRRITATION. IF SKIN IRRITATION BECOMES SEVERE, STOP USE AND CONSULT A DOCTOR.

DO NOT USE

- ON CHILDREN UNDER 12 YEARS OF AGE UNLESS DIRECTED BY A DOCTOR.

KEEP OUT OF REACH OF CHILDREN. IF SWALLOWED, GET MEDICAL HELP OR CONTACT A POISON CONTROL CENTER RIGHT AWAY.

DIRECTIONS

APPLY A SMALL AMOUNT AS A THIN LAYER ON THE AFFECTED AREA TWICE DAILY, OR USE AS DIRECTED BY A DOCTOR. IF NO IMPROVEMENT IS SEEN AFTER 3 MONTHS OF TREATMENT, USE OF THIS PRODUCT SHOULD BE DISCONTINUED. LIGHTENING EFFECT OF THIS PRODUCT MAY NOT BE NOTICEABLE WHEN USED ON VERY DARK SKIN. CHILDREN UNDER 12 YEARS OF AGE: DO NOT USE UNLESS DIRECTED BY A DOCTOR.

INACTIVE INGREDIENTS:

WATER, PROPYLENE GLYCOL, CETYL ALCOHOL, MINERAL OIL, GLYCERYL STEARATE, CETEARYL ALCOHOL, CETEARETH-20, POTATO STARCH MODIFIED, DIMETHICONE, FRAGRANCE, PHENOXYETHANOL, TRIMETHYLPROPANEDIOL/ADIPIC ACID COPOLYMER, LANOLIN, SODIUM METABISULFITE, METHYLPARABEN, CITRUS GRANDIS (GRAPEFRUIT) PEEL OIL, TETRASODIUM EDTA, PHOSPHOLIPIDS, TOCOPHERYL ACETATE, RETINYL ACETATE, ASCORBYL PALMITATE, CITRIC ACID.